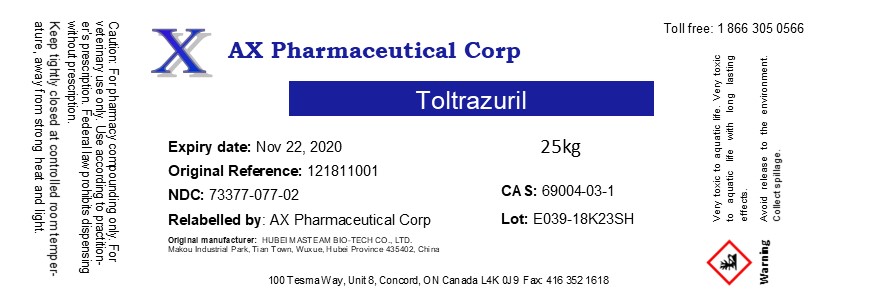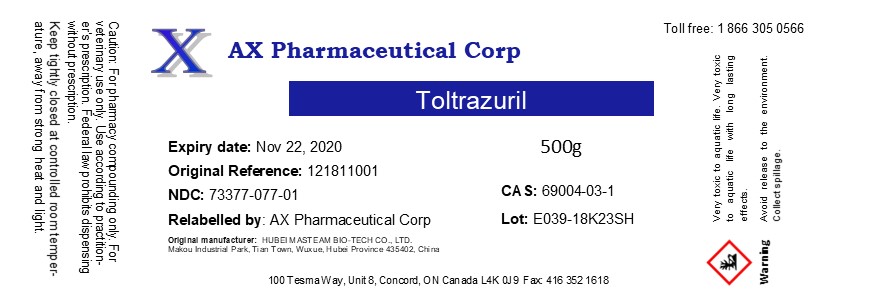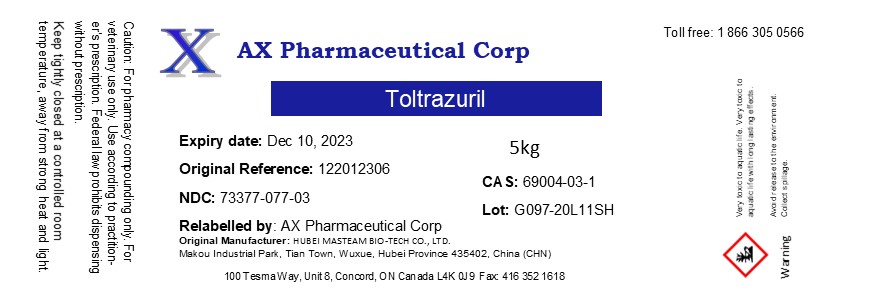 DRUG LABEL: Toltrazuril
NDC: 73377-077 | Form: POWDER
Manufacturer: AX Pharmaceutical Corp
Category: other | Type: BULK INGREDIENT - ANIMAL DRUG
Date: 20260116

ACTIVE INGREDIENTS: TOLTRAZURIL 1 kg/1 kg

Toltrazuril